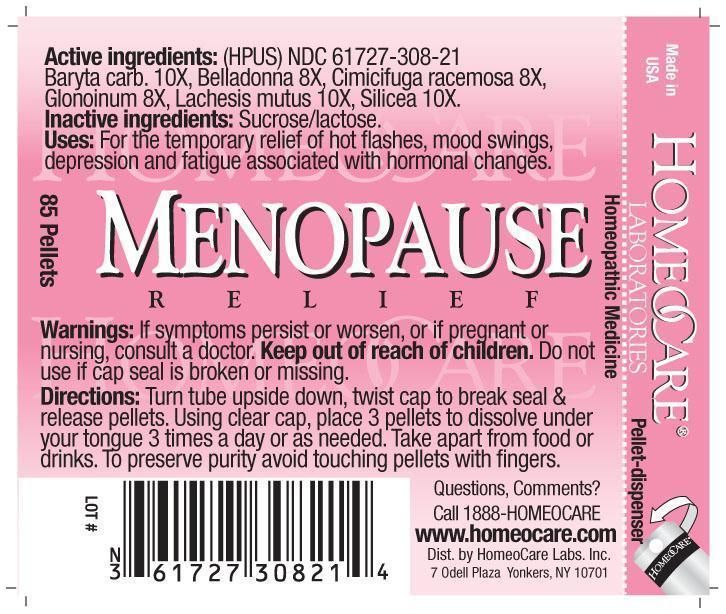 DRUG LABEL: Menopause Relief
NDC: 61727-308 | Form: PELLET
Manufacturer: Homeocare Laboratories
Category: homeopathic | Type: HUMAN OTC DRUG LABEL
Date: 20260112

ACTIVE INGREDIENTS: BARIUM CARBONATE 10 [hp_X]/4 g; ATROPA BELLADONNA 8 [hp_X]/4 g; BLACK COHOSH 8 [hp_X]/4 g; NITROGLYCERIN 8 [hp_X]/4 g; LACHESIS MUTA VENOM 10 [hp_X]/4 g; SILICON DIOXIDE 10 [hp_X]/4 g
INACTIVE INGREDIENTS: SUCROSE; LACTOSE

Menopause Relief

Active ingredients:

Baryta carb. 10X, Belladonna 8X, Cimicifuga racemosa 8X, Glonoinum 8X, Lachesis mutus 10X, Silicea 10X.

Inactive ingredients:

Sucrose, lactose.

Purpose:

For the temporary relief of hot flashes, mood swings, depression and fatigue associated with hormonal changes.

Keep out of reach of children.

Indications & Usage:

For the temporary relief of hot flashes, mood swings, depression and fatigue associated with hormonal changes.

Warnings:

If symptoms persist or worsen, or if pregnant or nursing, consult a doctor. Keep out of reach of children. Do not use if cap seal is broken or missing.

Dosage & Administration:

Turn tube upside down, twist cap to break seal & release pellets. Using clear cap, place 3 pellets to dissolve under your tongue 3 times a day or as needed. Take apart from food or drinks. To preserve purity avoid touching pellets with fingers.

Menopause Relief

Homeopathic Medicine

85 Pellets

hcl_label_menopause 2012.jpg